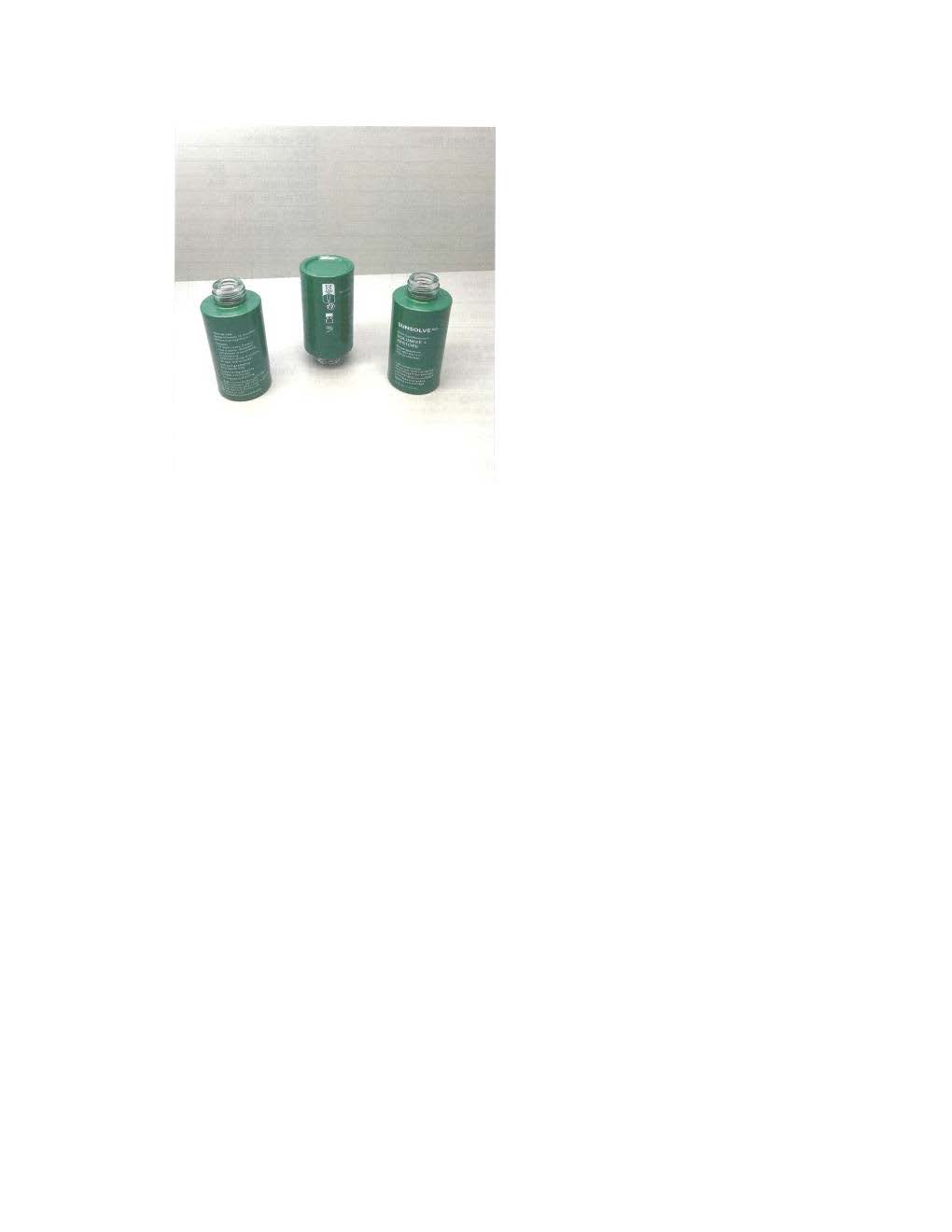 DRUG LABEL: Sunsovle MD Volumize and Restore
NDC: 84878-823 | Form: LOTION
Manufacturer: Sunsolve MD Inc
Category: otc | Type: HUMAN OTC DRUG LABEL
Date: 20251114

ACTIVE INGREDIENTS: ZINC OXIDE 110 mg/1 mL
INACTIVE INGREDIENTS: ETHYL STEARATE; CAPRYLYL GLYCOL; .ALPHA.-BISABOLOL, (+)-; POLYGLYCERYL-2 DIPOLYHYDROXYSTEARATE; SQUALANE; ISODODECANE; BUTYLOCTYL SALICYLATE; TOCOPHEROL; ALKYL (C12-15) BENZOATE; COCO-CAPRYLATE; ETHYL OLEATE; RUTIN; PENTAERYTHRITYL TETRA-DI-T-BUTYL HYDROXYHYDROCINNAMATE; POLYMETHYLSILSESQUIOXANE (4.5 MICRONS); CAPRYLIC/CAPRIC TRIGLYCERIDE; LIMNANTHES ALBA (MEADOWFOAM) SEED OIL; METHYLPROPANEDIOL; SILICON DIOXIDE; DISTEARDIMONIUM HECTORITE; BUTYROSPERMUM PARKII (SHEA) BUTTER UNSAPONIFIABLES; ETHYL PALMITATE; ISOHEXADECANE; C13-15 ALKANE; LECITHIN, SOYBEAN; ETHYL LINOLEATE

Sunsolve MD Volumize and Restore